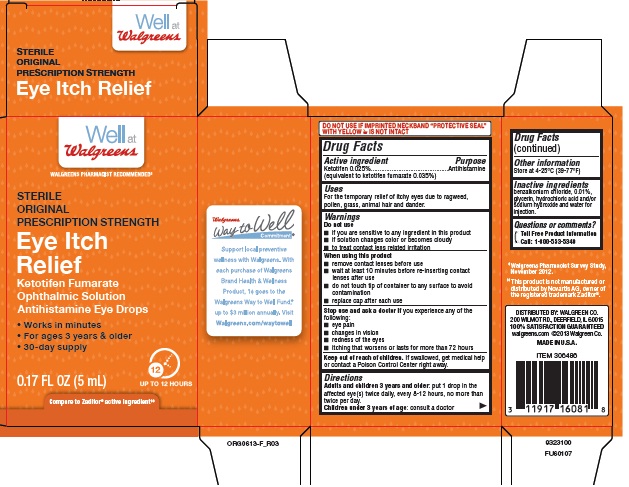 DRUG LABEL: EYE ITCH RELIEF
NDC: 0363-0610 | Form: SOLUTION/ DROPS
Manufacturer: Walgreens
Category: otc | Type: HUMAN OTC DRUG LABEL
Date: 20140923

ACTIVE INGREDIENTS: KETOTIFEN FUMARATE 0.25 mg/1 mL
INACTIVE INGREDIENTS: Benzalkonium Chloride; Glycerin; Hydrochloric Acid; Sodium Hydroxide; Water

Drug Facts

Active ingredient

Ketotifen (0.025%)

Purpose

Antihistamine

(equivalent to ketotifen fumarate 0.035%)

Uses

For the temporary relief of itchy eyes due to ragweed, pollen, grass, animal hair and dander.

Warnings

Do not use

- if you are sensitive to any ingredient in this product
- if solution changes color or becomes cloudy
- to treat contact lens related irritation

When using this product

- remove contact lenses before use
- wait at least 10 minutes before re-inserting contact lenses after use
- do not touch tip of container to any surface to avoid contamination
- replace cap after each use

Stop use and ask a doctor if you experience any of the following:

- eye pain
- changes in vision
- redness of the eyes
- itching that worsens or lasts for more than 72 hours

Keep out of reach of children.

If swallowed, get medical help or contact a Poison Control Center right away.

Directions

- Adults and children 3 years and older: put 1 drop in the affected eye(s) twice daily, every 8-12 hours, no more than twice per day.
- Children under 3 years of age: consult a doctor

Other information

- store at 4-25°C (39-77°F)

Inactive ingredients

benzalkonium chloride 0.01%, glycerin, hydrochloric acid and/or sodium hydroxide and water for injection.

Questions or comments?

Toll Free Product Information

Call: 1-800-553-5340

DISTRIBUTED BY: WALGREEN CO.

200 WILMOT RD., DEERFIELD, IL 60015

100% SATISFACTION GUARANTEED

walgreens.com ©2013 Walgreen Co.

MADE IN U.S.A.

ITEM 306486

9323100

FU60107

PACKAGE LABEL

Principal Display Panel

Well at

Walgreens

WALGREENS PHARMACIST RECOMMENDED‡

STERILE

ORIGINAL

PRESCRIPTION STRENGTH

Eye Itch

Relief

Ketotifen Fumarate

Ophthalmic Solution

Antihistamine Eye Drops

- Works in minutes
- For ages 3 years & older
- 30-day supply

0.17 FL OZ (5 mL)

12 UP TO 12 HOURS

Compare to Zaditor® active ingredient‡‡